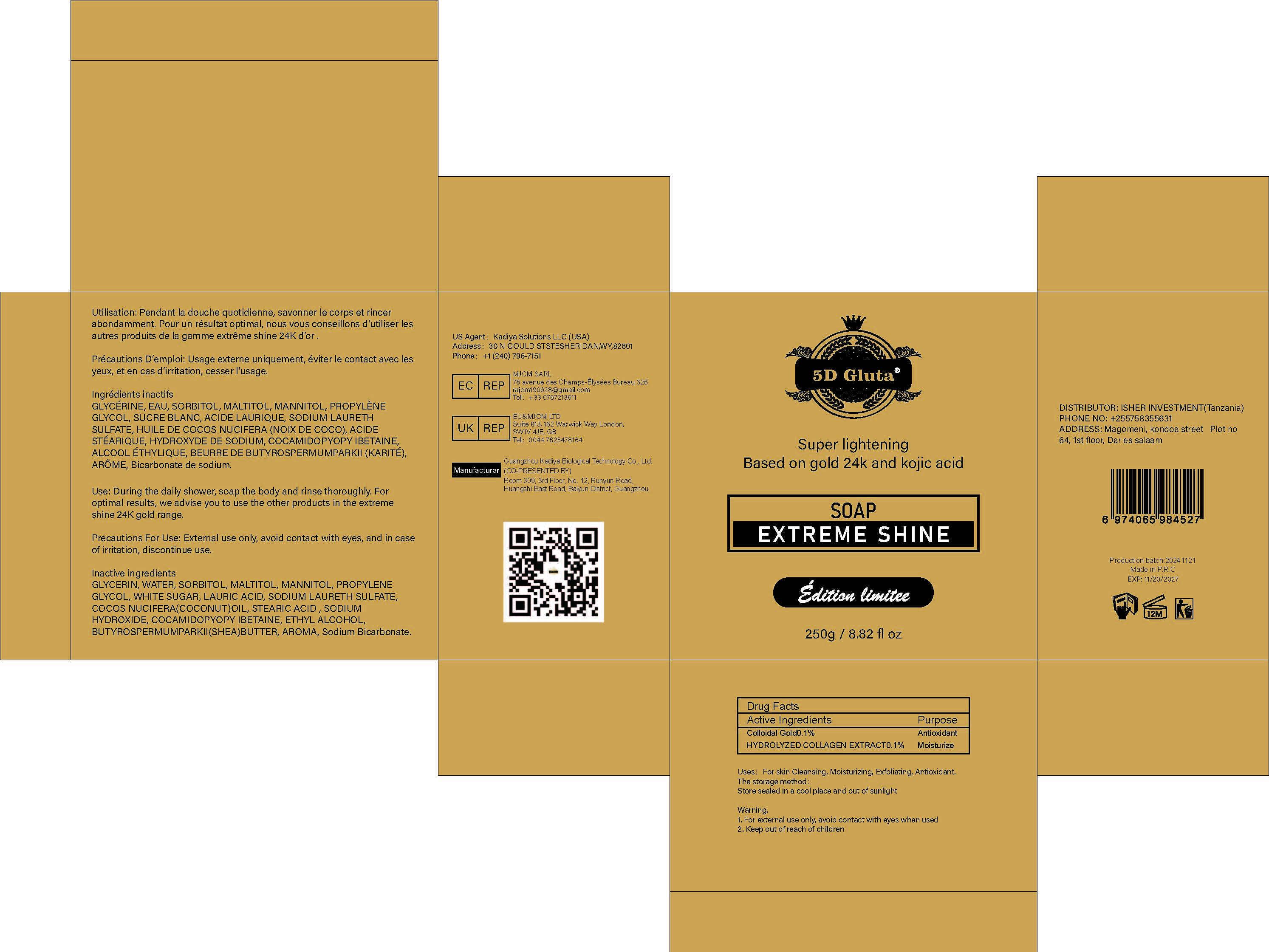 DRUG LABEL: SuperLighteningBasedonGold24kandKojicAcidSOAP
NDC: 84423-067 | Form: SOAP
Manufacturer: Guangzhou Kadiya Biotechnology Co., Ltd.
Category: otc | Type: HUMAN OTC DRUG LABEL
Date: 20250217

ACTIVE INGREDIENTS: COLLOIDAL GOLD 0.25 g/250 g
INACTIVE INGREDIENTS: GLYCERIN; SORBITOL; WATER; COCOS NUCIFERA (COCONUT) OIL; SODIUM LAURETH SULFATE; SODIUM HYDROXIDE; ALCOHOL; MANNITOL; SUCROSE; SODIUM BICARBONATE; PROPYLENE GLYCOL; BUTYROSPERMUM PARKII (SHEA) BUTTER; MALTITOL; LAURIC ACID; STEARIC ACID; COCAMIDOPROPYL BETAINE

PURPOSE

For skin Cleansing, Moisturizing, Exfoliating, Antioxidant

INACTIVE INGREDIENT

GLYCERIN，WATER，SORBITOL，MALTITOL，MANNITOL，PROPYLENE GLYCOL
，WHITE SUGAR，LAURIC ACID，SODIUM LAURETH SULFATE，COCOS NUCIFERA(COCONUT)OIL，STEARIC ACID ，SODIUM HYDROXIDE，COCAMIDOPYOPY IBETAINE，ETHYL ALCOHOL，BUTYROSPERMUMPARKII(SHEA)BUTTER，AROMA，Sodium Bicarbonate

Warning.
1、For external use only, avoid contact with eyes when used
2、Keep out of reach of children

INACTIVE INGREDIENT

Pendant la douche quotidienne, savonner le corps et rincerdabondamment.

DOSAGE AND ADMINISTRATION

After showering, apply evenly to your body

KEEP OUT OF REACH OF CHILDREN SECTION

ACTIVE INGREDIENT

Colloidal Gold0.1%
HYDROLYZED COLLAGEN EXTRACT0.1%

INDICATIONS AND USAGE

Dondant la doucho auetidionno eauonnor lo come ot rineorahondamment Pour un réeultat ontimal noue voue coneoillone d'utiliear leel autres produits de la namme extrême shine 24K dor

PACKAGE LABEL

Active Ingredients
Colloidal Gold0.1%
HYDROLYZED COLLAGEN EXTRACT0.1%

Uses：
For skin Cleansing, Moisturizing, Exfoliating, Antioxidant
The storage method：
Store sealed in a cool place and out of sunlight

Warning.
1、For external use only, avoid contact with eyes when used
2、Keep out of reach of children

Inactive ingredients：
GLYCERIN，WATER，SORBITOL，MALTITOL，MANNITOL，PROPYLENE GLYCOL
，WHITE SUGAR，LAURIC ACID，SODIUM LAURETH SULFATE，COCOS NUCIFERA(COCONUT)OIL，STEARIC ACID ，SODIUM HYDROXIDE，COCAMIDOPYOPY IBETAINE，ETHYL ALCOHOL，BUTYROSPERMUMPARKII(SHEA)BUTTER，AROMA，Sodium Bicarbonate